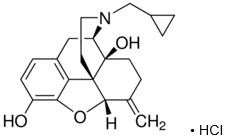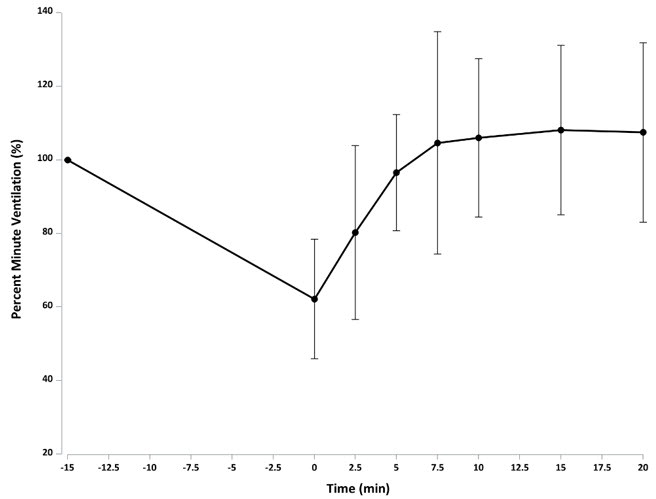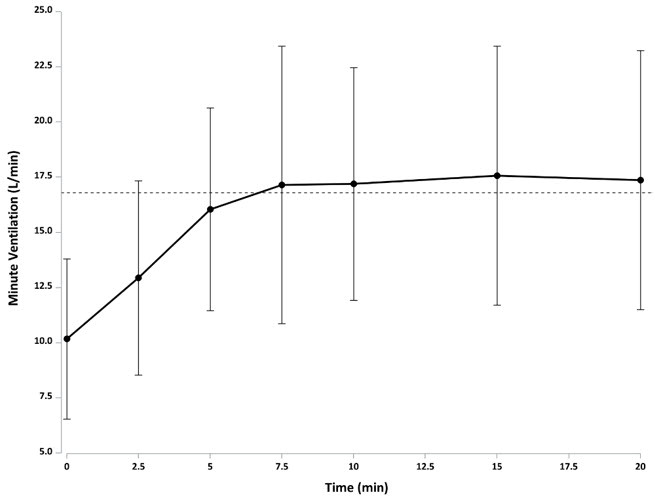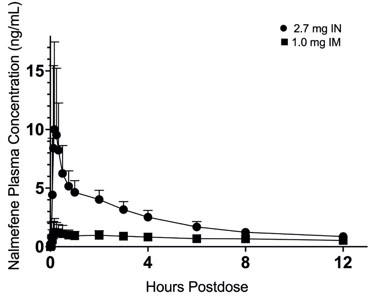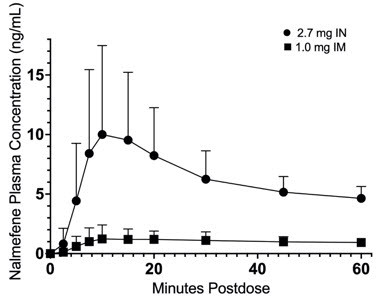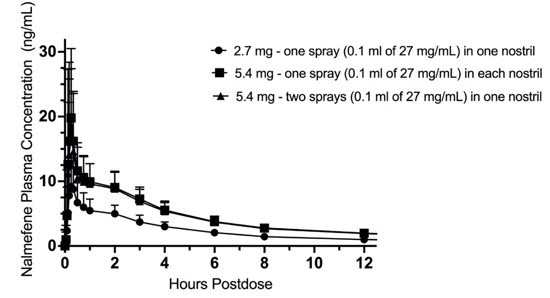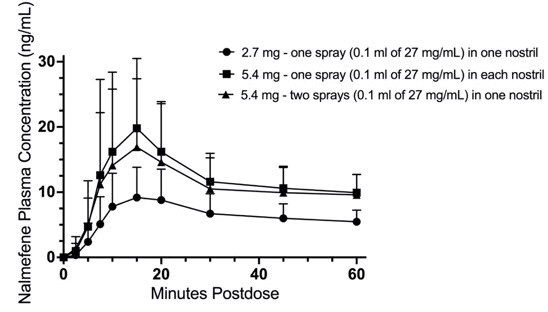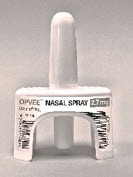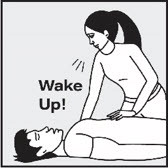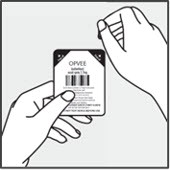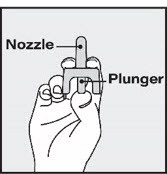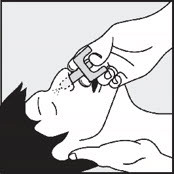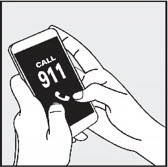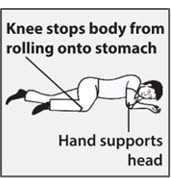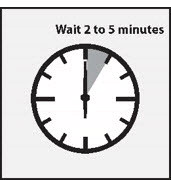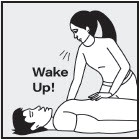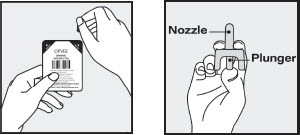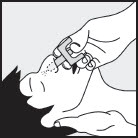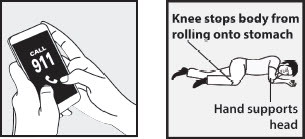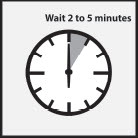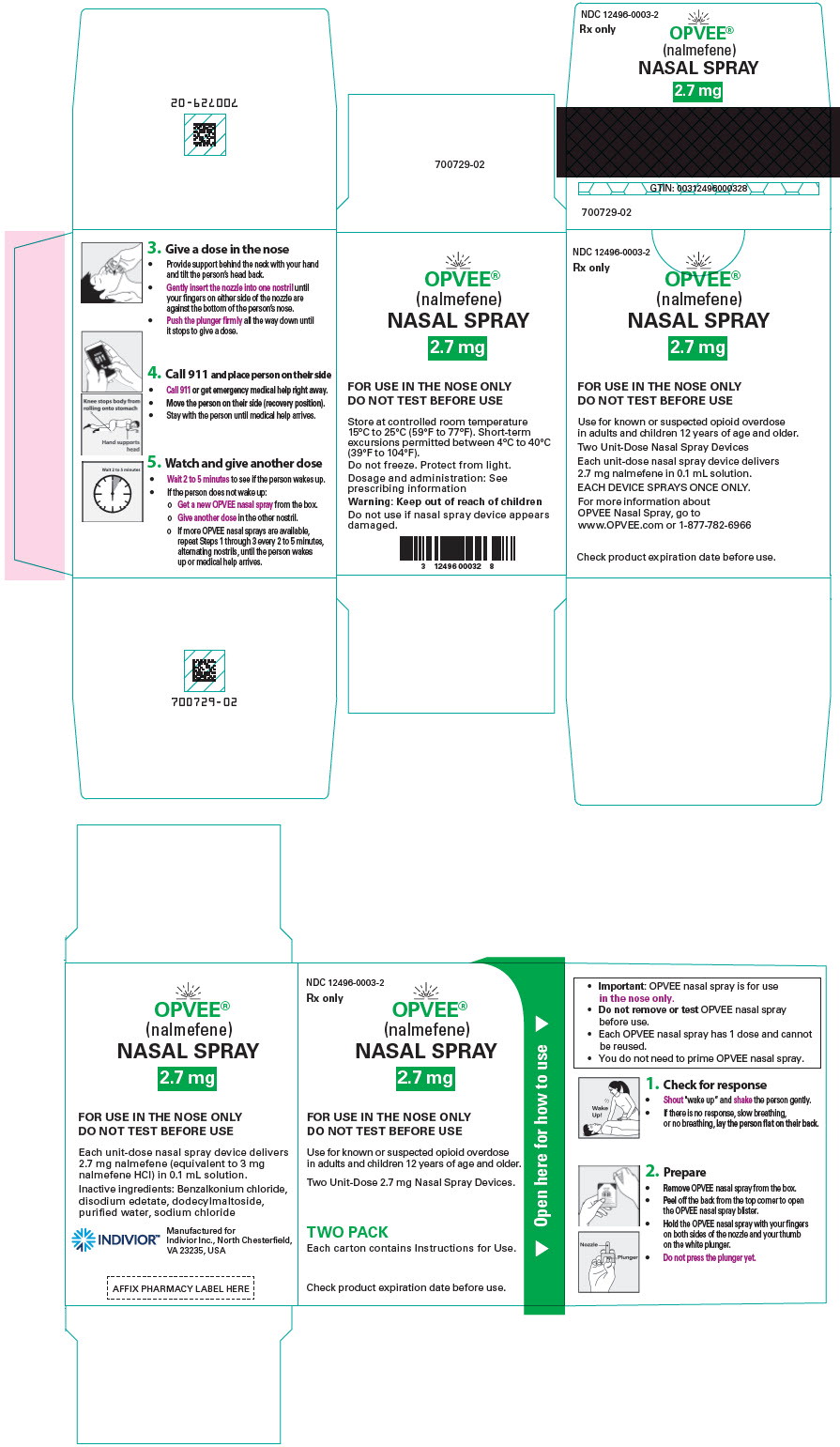 DRUG LABEL: OPVEE
NDC: 12496-0003 | Form: SPRAY
Manufacturer: Indivior Inc.
Category: prescription | Type: HUMAN PRESCRIPTION DRUG LABEL
Date: 20260108

ACTIVE INGREDIENTS: NALMEFENE HYDROCHLORIDE 2.7 mg/100 uL

HIGHLIGHTS OF PRESCRIBING INFORMATION These highlights do not include all the information needed to use OPVEE safely and effectively. See full prescribing information for OPVEE.
Prescribing Information - OPVEE®(nalmefene) nasal spray
Initial U.S. Approval: 1995

1 INDICATIONS AND USAGE

OPVEE nasal spray is an opioid antagonist indicated for the emergency treatment of known or suspected overdose induced by natural or synthetic opioids in adults and pediatric patients aged 12 years and older, as manifested by respiratory and/or central nervous system depression.

OPVEE nasal spray is intended for immediate administration as emergency therapy in settings where opioids may be present.

OPVEE nasal spray is not a substitute for emergency medical care.

2 DOSAGE AND ADMINISTRATION

- OPVEE nasal spray is for intranasal use only (2.1)
- Seek emergency care immediately after use (2.1)
- Administer a single spray of OPVEE nasal spray intranasally into nose. (2.2)
- Administer additional doses of OPVEE nasal spray, using a new nasal spray with each dose, if the patient does not respond or responds and then relapses into respiratory depression, additional doses of OPVEE nasal spray may be given every 2 to 5 minutes until emergency medical assistance arrives. (2.2)
- Additional supportive and/or resuscitative measures may be helpful while awaiting emergency medical assistance. (2.2)

3 DOSAGE FORMS AND STRENGTHS

Nasal spray: 2.7 mg of nalmefene in 0.1 mL (3)

4 CONTRAINDICATIONS

Hypersensitivity to nalmefene or to any of the other ingredients. (4)

5 WARNINGS AND PRECAUTIONS

- Risk of Recurrent Respiratory and Central Nervous System Depression: While the duration of action of nalmefene is as long as most opioids, a recurrence of respiratory depression is possible, therefore, keep patient under continued surveillance and administer repeat doses of OPVEE using a new nasal spray with each dose, as necessary, while awaiting emergency medical assistance (5.1)
- Limited Efficacy with Partial Agonists or Mixed Agonist/Antagonists: Reversal of respiratory depression caused by partial agonists or mixed agonists/antagonists, such as buprenorphine and pentazocine, may be incomplete. Larger or repeat doses may be required. (5.2)
- Precipitation of Severe Opioid Withdrawal: Use in patients who are opioid dependent may precipitate opioid withdrawal. In neonates, opioid withdrawal may be life-threatening if not recognized and properly treated. Monitor for the development of opioid withdrawal. (5.3)
- Risk of Cardiovascular (CV) Effects: Abrupt postoperative reversal of opioid depression may result in adverse CV effects. These events have primarily occurred in patients who had preexisting CV disorders or received other drugs that may have similar adverse CV effects. Monitor these patients closely in an appropriate healthcare setting after use of nalmefene hydrochloride. (5.3)
- Risk of Opioid Overdose from Attempts to Overcome the Blockade: Attempts to overcome opioid withdrawal symptoms caused by opioid antagonists with high or repeated doses of exogenous opioids may lead to opioid intoxication and death (5.4)

6 ADVERSE REACTIONS

Most common adverse reactions (incidence at least 2%) are nasal discomfort, headache, nausea, dizziness, hot flush, vomiting, anxiety, fatigue, nasal congestion, throat irritation, rhinalgia, decreased appetite, dysgeusia, erythema, and hyperhidrosis. (6)

To report SUSPECTED ADVERSE REACTIONS, contact Indivior Inc. at 1-877-782-6966 or FDA at 1-800-FDA-1088 or www.fda.gov/medwatch.

FULL PRESCRIBING INFORMATION

1 INDICATIONS AND USAGE

OPVEE nasal spray is indicated for the emergency treatment of known or suspected overdose induced by natural or synthetic opioids in adults and pediatric patients aged 12 years and older, as manifested by respiratory and/or central nervous system depression.

OPVEE nasal spray is intended for immediate administration as emergency therapy in settings where opioids may be present.

OPVEE nasal spray is not a substitute for emergency medical care.

2 DOSAGE AND ADMINISTRATION

2.1 Important Administration Instructions

- OPVEE is for intranasal use only.
- The device is ready to use. No device assembly is required.
- Do not prime or test prior to administration. OPVEE nasal spray delivers its entire contents automatically, upon activation.
- Do not attempt to reuse OPVEE. Each unit-dose device contains a single dose of nalmefene and cannot be reused.
- No device assembly is required.
- Because treatment of suspected opioid overdose must be performed by someone other than the patient, instruct the prescription recipient to inform those around them about the presence of OPVEE nasal spray and the Instructions for Use.
- Instruct the patient or caregiver to read the Instructions for Useat the time they receive a prescription for OPVEE nasal spray. Emphasize the following instructions to the patient or caregiver:
- Administer OPVEE nasal spray as quickly as possiblebecause prolonged respiratory depression may result in damage to the central nervous system or death.
- Always seek emergency medical assistance after administration of the first dose of OPVEE nasal spray in the event of a suspected, potentially life-threatening opioid emergency. Keep the patient under continued surveillance until emergency personnel arrive.
- Additional doses of OPVEE nasal spray may be required until emergency medical assistance becomes available.
- Re-administer OPVEE nasal spray, using a new nasal spray, in the nose, every 2 to 5 minutes if the patient does not respond or responds and then relapses into respiratory depression.
- Administer OPVEE nasal spray according to the printed instructions on the Quick Start Guideand the Instructions for Use.
  - Place the patient in the supine position. Prior to administration, be sure the device nozzle is inserted in the nose of the patient and provide support to the back of the neck to allow the head to tilt back. Do not prime or test the device prior to administration.
  - To administer the dose, press firmly on the device plunger and remove the device nozzle from the nose after use.
  - If the patient responds by waking up to the voice or touch or starts breathing normally, place the patient on their side (recovery position) as shown in the Instructions for Useand call for emergency medical assistance immediately after administration of the first dose of OPVEE nasal spray.

2.2 Dosing in Adults and Pediatric Patients aged 12 years and older

Initial Dosing:

The recommended initial dose of OPVEE nasal spray in adults and pediatric patients aged 12 years and older is one spray delivered by intranasal administration, which delivers 2.7 mg of nalmefene.

Repeat Dosing:

Seek emergency medical assistance as soon as possible after intranasal administration of the first dose of OPVEE nasal spray. The requirement for repeat doses of OPVEE nasal spray (2.7 mg) depends upon the amount, type, and route of administration of the opioid being antagonized.

If the patient responds to OPVEE nasal spray and relapses back into respiratory depression before emergency assistance arrives, administer an additional dose of OPVEE in the opposite nostril using a new OPVEE nasal spray and continue surveillance of the patient.

If the desired response is not obtained after 2 to 5 minutes, administer an additional dose of OPVEE using a new OPVEE nasal spray device. If there is still no response and additional doses are available, administer additional doses of OPVEE nasal spray every 2 to 5 minutes using a new OPVEE nasal spray device with each dose until emergency medical assistance arrives.

Additional supportive and/or resuscitative measures may be helpful while awaiting emergency medical assistance.

2.3 Dosing Modifications due to Partial Agonists or Mixed Agonists/Antagonists

Reversal of respiratory depression by partial agonists or mixed agonist/antagonists, such as buprenorphine and pentazocine, may be incomplete and require repeated administration of OPVEE nasal spray using a new nasal spray device [see Warnings and Precautions (5.2)] .

3 DOSAGE FORMS AND STRENGTHS

Nasal spray: 2.7 mg nalmefene per device. Each unit-dose nasal spray device delivers a single spray containing 2.7 mg of nalmefene.

4 CONTRAINDICATIONS

OPVEE nasal spray is contraindicated in patients known to be hypersensitive to nalmefene or to any of the other ingredients.

5 WARNINGS AND PRECAUTIONS

5.1 Risk of Recurrent Respiratory and Central Nervous System Depression

Respiratory depression in the community overdose setting may be complex and involve the effects of multiple or unknown drugs, some of which may be long-acting opioids. While the duration of action of nalmefene is as long as most opioids, a recurrence of respiratory depression is possible, even after an apparently adequate initial response to OPVEE nasal spray treatment [See Clinical Pharmacology, Pharmacodynamics (12.3)] . Therefore, it is necessary to seek emergency medical assistance immediately after administration of the first dose of OPVEE nasal spray and to keep the patient under continued surveillance. A second dose may be necessary if there is recurrence of symptoms of opioid overdose. Additional supportive and/or resuscitative measures may be helpful while awaiting emergency medical assistance [see Dosage and Administration (2.2)].

5.2 Risk of Limited Efficacy with Partial Agonists or Mixed Agonist/Antagonists

Reversal of respiratory depression by partial agonists or mixed agonist/antagonists such as buprenorphine and pentazocine, may be incomplete. Repeat doses of OPVEE nasal spray may be required to antagonize buprenorphine because the latter has a long duration of action due to its slow rate of binding and subsequent slow dissociation from the opioid receptor [see Dosage and Administration (2.3)] . Buprenorphine antagonism is characterized by a gradual onset of the reversal effects and a decreased duration of action of the normally prolonged respiratory depression.

5.3 Precipitation of Severe Opioid Withdrawal

The use of OPVEE in patients who are opioid dependent may precipitate opioid withdrawal characterized by the following signs and symptoms: body aches, diarrhea, tachycardia, fever, runny nose, sneezing, piloerection, sweating, yawning, nausea or vomiting, nervousness, restlessness or irritability, shivering or trembling, abdominal cramps, weakness, and increased blood pressure.

Abrupt postoperative reversal of opioid depression after using OPVEE may result in nausea, vomiting, sweating, tremulousness, tachycardia, hypotension, hypertension, seizures, ventricular tachycardia and fibrillation, pulmonary edema, and cardiac arrest. Death, coma, and encephalopathy have been reported as sequelae of these events. These events have primarily occurred in patients who had pre-existing cardiovascular disorders or received other drugs that may have similar adverse cardiovascular effects. After use of OPVEE, monitor patients with pre-existing cardiac disease or patients who have received medications with potential adverse cardiovascular effects for hypotension, ventricular tachycardia or fibrillation, and pulmonary edema in an appropriate healthcare setting. It has been suggested that the pathogenesis of pulmonary edema associated with the use of nalmefene is similar to neurogenic pulmonary edema, i.e., a centrally mediated massive catecholamine response leading to a dramatic shift of blood volume into the pulmonary vascular bed resulting in increased hydrostatic pressures.

OPVEE is not indicated for use in patients less than 12 years of age. In neonates, opioid withdrawal may be life-threatening if not recognized and properly treated and may include the following signs and symptoms: convulsions, excessive crying, and hyperactive reflexes. Monitor the patient for the development of the signs and symptoms of opioid withdrawal. There may be clinical settings, particularly the postpartum period in neonates with known or suspected exposure to maternal opioid use, where it is preferable to avoid the abrupt precipitation of opioid withdrawal symptoms. In these settings, use an alternative, opioid antagonist product that can be titrated to effect and, where applicable, dosed according to weight. [see Use in Specific Populations (8.4)] .

5.4 Risk of Opioid Overdose from Attempts to Overcome the Blockade

OPVEE is unlikely to produce acute withdrawal symptoms in non-opioid dependent patients. The use of OPVEE nasal spray in patients who are opioid dependent may precipitate opioid withdrawal. Attempting to overcome opioid withdrawal symptoms caused by opioid antagonists with high or repeated doses of exogenous opioids could lead to opioid intoxication and death. Inform patients of the potential consequences of trying to overcome the opioid blockade. Get emergency medical assistance as soon as possible after use of OPVEE nasal spray regardless of withdrawal symptoms.

6 ADVERSE REACTIONS

The following serious adverse reactions are discussed elsewhere in the labeling:

- Recurrent Respiratory and Central Nervous System Depression [see Warnings and Precautions (5.1)]
- Precipitation of Severe Opioid Withdrawal [see Warnings and Precautions (5.3)]

6.1 Clinical Trials Experience

Because clinical trials are conducted under widely varying conditions, adverse reaction rates observed in the clinical trials of a drug cannot be directly compared to the rates in clinical trials of another drug and may not reflect the rates observed in practice.

The safety of OPVEE nasal spray is supported by safety and pharmacokinetic studies of OPVEE nasal spray in healthy subjects in a normal state and under steady state opioid agonism. The following adverse reactions were observed.

In a pharmacokinetic study of 66 healthy adult volunteers exposed to one spray of OPVEE nasal spray in one nostril the most common adverse reactions were: nasal discomfort and dizziness.

In a second pharmacokinetic study of 24 healthy adult volunteers exposed to one spray of OPVEE nasal spray in one nostril, two sprays of OPVEE nasal spray in one nostril or one spray of OPVEE nasal spray in each nostril, the most common adverse reactions were: rhinalgia, nasal congestion, nasal discomfort and nausea.

In a pharmacodynamic study of 61 healthy adult volunteers exposed to one spray of OPVEE nasal spray in one nostril, the most common adverse reactions were: headache, nausea, hot flush and dizziness.

Table 1: Relative Frequencies of Treatment-Related Common Adverse Events That Occurred in Greater Than 1% of Healthy Adult Volunteers
 | Nalmefene 2.7 mg |  |  | Nalmefene 5.4 mg
System Organ Class Preferred Term | Total 2.7 mg N=150 n (%) | PD Study N=61 n (%) | PK Studies N=89 n (%) | PK Study (1 spray in each nostril) N=23 n (%) | PK Study (2 sprays in one nostril) N=24 n (%)
Respiratory, thoracic and mediastinal disorders
Nasal discomfort | 43 (28.7%) | 5 (8.2%) | 38 (42.7%) | 3 (13.0%) | 3 (12.5%)
Nasal congestion | 6 (4.0%) | 2 (3.3%) | 4 (4.5%) | 1 (4.3%) | 4 (16.7%)
Throat irritation | 6 (4.0%) | 3 (4.9%) | 3 (3.4%) | 0 | 0
Rhinalgia | 4 (2.7%) | 1 (1.6%) | 3 (3.4%) | 2 (8.7%) | 6 (25.0%)
Dyspnea | 2 (1.3%) | 2 (3.3%) | 0 | 0 | 0
Oropharyngeal pain | 2 (1.3%) | 2 (3.3%) | 0 | 1 (4.3%) | 1 (4.2%)
Nervous system disorders
Headache | 40 (26.7%) | 34 (55.7%) | 6 (6.7%) | 1 (4.3%) | 0
Dizziness | 14 (9.3%) | 9 (14.8%) | 5 (5.6%) | 0 | 1 (4.2%)
Dysgeusia | 3 (2.0%) | 2 (3.3%) | 1 (1.1%) | 0 | 0
Paresthesia | 2 (1.3%) | 2 (3.3%) | 0 | 1 (4.3%) | 1 (4.2%)
Presyncope | 0 | 0 | 0 | 1 (4.3%) | 0
Gastrointestinal disorders
Nausea | 25 (16.7%) | 22 (36.1%) | 3 (3.4%) | 5 (21.7%) | 1 (4.2%)
Vomiting | 9 (6.0%) | 7 (11.5%) | 2 (2.2%) | 1 (4.3%) | 0
Abdominal pain | 2 (1.3%) | 1 (1.6%) | 1 (1.1%) | 0 | 0
Dry mouth | 1 (0.7%) | 1 (1.6%) | 0 | 1 (4.3%) | 0
Constipation | 0 | 0 | 0 | 0 | 1 (4.2%)
Vascular disorders
Hot flush | 12 (8.0%) | 12 (19.7%) | 0 | 0 | 0
Psychiatric disorders
Anxiety | 7 (4.7%) | 7 (11.5%) | 0 | 0 | 0
Agitation | 2 (1.3%) | 2 (3.3%) | 0 | 0 | 0
Claustrophobia | 2 (1.3%) | 2 (3.3%) | 0 | 0 | 0
Insomnia | 1 (0.7%) | 0 | 1 (1.1%) | 1 (4.3%) | 0
General disorders and administration site conditions
Fatigue | 6 (4.0%) | 3 (4.9%) | 3 (3.4%) | 0 | 0
Chills | 2 (1.3%) | 2 (3.3%) | 0 | 0 | 0
Chest discomfort | 0 | 0 | 0 | 1 (4.3%) | 0
Skin and subcutaneous tissue disorders
Erythema | 3 (2.0%) | 0 | 3 (3.4%) | 1 (4.3%) | 1 (4.2%)
Hyperhidrosis | 3 (2.0%) | 3 (6.6%) | 0 | 0 | 1 (4.2%)
Urticaria | 0 | 0 | 0 | 0 | 1 (4.2%)
Metabolism and nutrition disorders
Decreased appetite | 3 (2.0%) | 2 (3.3%) | 1 (1.1%) | 0 | 0
Infections and infestations
Rhinitis | 1 (0.7%) | 0 | 1 (1.1%) | 1 (4.3%) | 0
Eye disorders
Dry eye | 0 | 0 | 0 | 1 (4.3%) | 0
Cardiac disorders
Tachycardia | 0 | 0 | 0 | 1 (4.3%) | 0
PK Studies OPNT003-PK-001 + OPNT003-PK-002 and PD Study OPNT003-OOD-001

Adverse reaction information was obtained following administration of nalmefene injection to 152 normal volunteers and in controlled clinical trials to 1127 patients for the treatment of opioid overdose or for postoperative opioid reversal.

Table 2. Relative Frequencies of Common Adverse Reactions with an Incidence Greater than 1% (all patients, all clinical settings)
Adverse Reaction | Nalmefene | Placebo
Adverse Reaction | N=1127 | N=77
Nausea | 18% | 6%
Vomiting | 9% | 4%
Tachycardia | 5% | -
Hypertension | 5% | -
Postoperative Pain | 4% | N/A
Fever | 3% | -
Dizziness | 3% | 1%
Headache | 1% | 4%
Chills | 1% | -
Hypotension | 1% | -
Vasodilatation | 1% | -

Incidence less than 1%

Cardiovascular: Bradycardia, arrhythmia
Digestive: Diarrhea, dry mouth
Nervous System: Somnolence, depression, agitation, nervousness, tremor, confusion, withdrawal syndrome, myoclonus
Respiratory: Pharyngitis
Skin: Pruritus
Urogenital: Urinary retention

The incidence of adverse events was highest in patients who received more than the recommended dose of nalmefene injection.

6.2 Postmarketing Experience

The following adverse reactions have been identified during post-approval use of nalmefene. Because these reactions are reported voluntarily from a population of uncertain size, it is not always possible to reliably estimate their frequency or establish a causal relationship to drug exposure.

Abrupt reversal of opioid depression using nalmefene in both postoperative and emergency department settings has resulted in nausea, vomiting, sweating, tremulousness, seizures, and cardiovascular instability including tachycardia, hypotension, hypertension, ventricular tachycardia and fibrillation, pulmonary edema, and cardiac arrest. Death, coma, and encephalopathy have been reported as sequelae of these events. These events have primarily occurred in patients who had pre-existing cardiovascular disorders or received other drugs that may have similar adverse cardiovascular effects.

In persons who were physically dependent on opioids, abrupt reversal of opioid effects has precipitated an acute withdrawal syndrome. Signs and symptoms have included: body aches, fever, sweating, runny nose, sneezing, piloerection, yawning, weakness, shiver or trembling, nervousness, restlessness or irritability, diarrhea, nausea or vomiting, abdominal cramps, increased blood pressure, tachycardia. In some patients, there may be aggressive behavior upon abrupt reversal of an opioid overdose. In the neonate, opioid withdrawal symptoms also included convulsions, excessive crying, and hyperactive reflexes.

8 USE IN SPECIFIC POPULATIONS

8.1 Pregnancy

Risk Summary

Life-sustaining therapy for opioid overdose should not be withheld (see Clinical Considerations). There are no available data on nalmefene use in pregnant women to evaluate for a drug-associated risk of major birth defects or miscarriage. In animal reproduction studies, no embryotoxic effects on embryo-fetal development were observed in rats and rabbits treated with nalmefene at exposures at least 6 times (rats) and up to 20 times (rabbits) the exposure at two human nasal doses of 5.4 mg (see Data) .

The background risk of major birth defects and miscarriage for the indicated population is unknown. All pregnancies have a background risk of birth defect, loss, or other adverse outcomes. In the U.S. general population, the estimated background risk of major birth defects and miscarriage in clinically recognized pregnancies is 2% to 4% and 15% to 20%, respectively.

Clinical Considerations

Disease-associated maternal and/or embryo/fetal risk

An opioid overdose is a medical emergency and can be fatal for the pregnant woman and fetus if left untreated. Treatment with OPVEE for opioid overdose should not be withheld because of potential concerns regarding the effects of OPVEE on the fetus.

Data

Animal Data

Reproduction studies have been performed in rats (up to 1200 mg/m^2/day) and rabbits (up to 2400 mg/m^2/day) by oral administration of nalmefene and in rabbits by intravenous administration up to 96 mg/m^2/day. No effects on embryo-fetal development were observed at exposures at least 6 times (rats) and up to 20 times (rabbits) the exposure corresponding to a human dose of 5.4 mg (two nalmefene nasal sprays) on an AUC basis. The treatment in rats did not affect offspring survival.

8.2 Lactation

Risk Summary

There are no data on the presence of nalmefene and its metabolites in human milk, the effects of nalmefene on the breastfed child, or the effects on milk production. Nalmefene and its metabolites are present in rat milk (see Data). When a drug is present in animal milk, it is likely that the drug will be present in human milk.

Data

Nalmefene and its metabolites were secreted into rat milk, reaching concentrations approximately three times those in plasma at one hour and decreasing to about half the corresponding plasma concentrations by 24 hours following bolus administration. The concentration of nalmefene in animal milk does not necessarily predict the concentration of drug in human milk.

8.4 Pediatric Use

The safety and effectiveness of OPVEE nasal spray for the emergency treatment of known or suspected opioid overdose in adults and pediatric patients aged 12 years and older, as manifested by respiratory and/or central nervous system depression, have been established.

Use for this indication in this age group is supported by adult studies and pharmacokinetic simulation [see Clinical Pharmacology (12.3)] . There have been no studies conducted to evaluate the use of OPVEE nasal spray in pediatric patients.

The safety and effectiveness of OPVEE nasal spray for the emergency treatment of known or suspected opioid overdose, as manifested by respiratory and/or central nervous system depression have not been established in pediatric patients younger than 12 years of age.

8.5 Geriatric Use

Clinical studies of OPVEE nasal spray did not include subjects aged 65 and over. Other reported clinical experience has not identified differences in responses between the elderly and younger patients. Geriatric patients have a greater frequency of decreased hepatic, renal, or cardiac function and of concomitant disease or other drug therapy. Therefore, the systemic exposure of nalmefene can be higher in these patients.

8.6 Hepatic Impairment

Hepatic impairment substantially reduces the clearance of nalmefene [see Clinical Pharmacology (12.3)]. For single episodes of opioid antagonism, adjustment of OPVEE nasal spray dosage is not required.

8.7 Renal Impairment

Renal impairment substantially reduces the clearance of nalmefene [see Clinical Pharmacology (12.3)]. For single episodes of opioid antagonisms, adjustment of OPVEE nasal spray dosage is not required.

11 DESCRIPTION

OPVEE (nalmefene) nasal spray is a pre-filled, unit-dose intranasal spray.

Nalmefene, an opioid antagonist, is a 6-methylene analogue of naltrexone. The molecular structure of nalmefene is presented below:

Molecular Formula: C21H25NO3∙HCl

Molecular Weight: 375.9, CAS # 58895-64-0

Chemical Name: 17-(Cyclopropylmethyl)-4,5α-epoxy-6-methylenemorphinan-3,14-diol, hydrochloride salt.

Nalmefene is a white to off-white crystalline powder which is freely soluble in methanol and water, with a pK of 7.63.

Each OPVEE nasal spray unit delivers 2.7 mg nalmefene (equivalent to 3mg nalmefene hydrochloride) in 0.1 mL solution.

Inactive ingredients include benzalkonium chloride, disodium ethylenediaminetetraacetate, dodecylmaltoside, sodium chloride, and purified water. The pH range is 4.1 to 4.9.

12 CLINICAL PHARMACOLOGY

12.1 Mechanism of Action

OPVEE is an antagonist at opioid receptors.

12.2 Pharmacodynamics

Nalmefene reverses the effects of natural and synthetic opioids, including respiratory depression, sedation, and hypotension. Pharmacodynamic studies have shown that nalmefene injection has a longer duration of action than naloxone injection at fully reversing doses. Nalmefene has no opioid agonist activity.

The effect of 2.7 mg OPVEE on remifentanil-induced respiratory depression in an experimental ventilatory-response to hypercapnia model, assessed by changes in minute ventilation (MV), was evaluated in sixty-one opioid-experienced, non-dependent subjects. In this study subjects started receiving a hypercapnic gas mixture (50% O2, 43% N2, 7% CO2) at -25 minutes. Just prior to initiation of remifentanil infusion at -15 minutes is the baseline MV (marked as 100% in Figure 1 and marked as observed data as liters/minute in Figure 2). Fifteen minutes after initiating remifentanil infusion, nadir in minute ventilation is observed at time zero, at which point OPVEE was administered. The subjects were then monitored for changes in MV over 120 minutes. Following OPVEE administration the time to onset of effect, that is onset of reversal of respiratory depression, was observed between 2.5 to 5 minutes (Figure 1 and Figure 2). At 5 minutes the estimated mean increase in minute ventilation was 5.745 L/min (Figure 2). Full recovery of respiratory drive was noted between 5 and 15 minutes after OPVEE administration (Figure 1 and Figure 2).

Figure 1: Percentage recovery of respiratory drive after infusion of remifentanil in CO2 stimulated minute ventilation (mean +/- standard deviation) in adult healthy volunteers treated with OPVEE (nalmefene) nasal spray

Figure 2: Reversal of Remifentanil-Induced Respiratory Depression (Mean Minute Ventilation +/- Standard Deviation) by OPVEE (nalmefene) nasal spray

Remifentanil (an initial bolus of 0.5 µg/kg dose followed by an infusion rate of 0.175 µg/kg/min) was administered for 15 min prior to test agents and continued for the duration of the study. The dashed line represents the mean minute ventilation (MV) prior to remifentanil administration.

Based on population pharmacokinetic/pharmacodynamic model simulations, the EC50 (drug concentration at which pharmacological effect is half maximum change in response) was 1.50 ng/mL for OPVEE following a single 2.7 mg administration. The time to reach EC50 was 4 minutes for OPVEE. The plasma concentrations remained above the EC50 for 5.94 hours for OPVEE.

Nalmefene is not known to produce respiratory depression, psychotomimetic effects, or pupillary constriction. No pharmacological activity was observed when nalmefene was administered in the absence of opioid agonists.

Nalmefene has not been shown to produce tolerance, physical dependence, or abuse potential.

Nalmefene can produce acute withdrawal symptoms in individuals who are opioid dependent.

12.3 Pharmacokinetics

In a pharmacokinetic study (OPNT003-PK-001) in 68 healthy adult subjects, the relative bioavailability of one 2.7 mg OPVEE nasal spray in one nostril (0.1 mL of 27 mg/mL nalmefene), was compared to a single dose of nalmefene 1.0 mg administered as an intramuscular injection. Subjects remained fully supine and were instructed to hold their breath during the intranasal spray administration. The pharmacokinetic parameters obtained in this study are shown in Table 3 and the plasma concentration time profiles of nalmefene are presented in Figure 3.

Table 3: Geometric Mean (CV%) PK Parameters of Nalmefene after Intranasal (IN) Administration of 2.7 mg OPVEE nasal spray and Intramuscular (IM) Administration of 1.0 mg of Nalmefene
Parameter | OPVEE | Nalmefene IM
Tmax(h) [T max presented as median (range)] | 0.250 (0.0833-2.00) | 0.33 (0.117-18.0)
Cmax(ng/mL) [Arithmetic mean] | 10.4 (62.6) | 1.50 (59.4)
AUC0-2.5min(ng-hr/mL) | 0.00763 (233) | 0.00168 (186)
AUC0-5min(ng-hr/mL) | 0.0599 (201) | 0.0102 (142)
AUC0-10min(ng-hr/mL) | 0.523 (124) | 0.0639 (118)
AUC0-15min(ng-hr/mL) | 1.20 (94.2) | 0.142 (98.6)
AUC0-20min(ng-hr/mL) | 1.89 (77.2) | 0.228 (84.5)
AUC0-30min(ng-hr/mL) | 3.07 (60.4) | 0.405 (69.2)
AUC0-inf(ng-hr/mL) | 40.6 (22.0) | 16.8 (18.7)
Frel | 0.806 (10.9) | NA
T½(h) | 11.4 (20.8) | 10.6 (18.5)
NA Not applicable

Figure 3: Mean Plasma Concentration-Time Profiles of Nalmefene (a) 0-12 hours and (b) 0-60 minutes Following Intranasal (IN) Administration of OPVEE nasal spray (2.7 mg) and Intramuscular (IM) Injection of Nalmefene (1.0 mg)

(a)

(b)

Values represent the mean and standard deviation (n=68)

In a second pharmacokinetic study (OPNT003-PK-002) in 24 healthy adult subjects, one 2.7 mg OPVEE nasal spray in one nostril was compared with two 2.7 mg OPVEE nasal sprays in one nostril and one 2.7 mg OPVEE nasal spray in each nostril. Subjects remained fully supine and were instructed to hold their breath during the intranasal spray administration. The pharmacokinetic parameters obtained in this study are shown in Table 4 and the plasma concentration time profiles of nalmefene are presented in Figure 4.

Table 4: Geometric Mean (CV%) PK Parameters of Nalmefene After Intranasal (IN) Dose of 2.7 mg Nalmefene (One OPVEE nasal spray in One Nostril), IN Dose of 5.4 mg Nalmefene (One OPVEE nasal spray in Each Nostril) and IN Dose of 5.4 mg Nalmefene (Two OPVEE nasal sprays in One Nostril)
Parameter | OPVEE 2.7mg (one spray) | OPVEE 5.4mg (one spray in each nostril) | OPVEE 5.4mg (two sprays in one nostril)
Tmax(h) [T max presented as median (range)] | 0.267 (0.167-2.03) | 0.250 (0.117-3.00) | 0.250 (0.117-2.03)
Cmax(ng/mL) | 9.75 (49.4) | 18.9 (88.0) | 16.1 (62.9)
AUC0-2.5min(ng-hr/mL) | 0.00594 (134) | 0.0163 (217) | 0.0172 (117)
AUC0-5min(ng-hr/mL) | 0.0446 (99.6) | 0.110 (161) | 0.108 (92.9)
AUC0-10min(ng-hr/mL) | 0.388 (72.1) | 0.828 (102) | 0.717 (93.2)
AUC0-15min(ng-hr/mL) | 0.999 (65.9) | 2.08 (81.8) | 1.73 (83.0)
AUC0-20min(ng-hr/mL) | 1.66 (61.3) | 3.42 (69.9) | 2.85(74.3)
AUC0-30min(ng-hr/mL) | 2.83 (56.0) | 5.63 (57.7) | 4.78 (60.8)
AUC0-inf(ng-hr/mL) | 45.8 (21.7) | 88.1 (18.3) | 83.8 (22.0)
T½(h) [Arithmetic mean] | 11.4 (22.0) | 11.3 (16.6) | 11.3 (16.5)

Figure 4: Mean Plasma Concentration of Nalmefene, (a) 0-12 hours and (b) 0-60 minutes Following Intranasal (IN) Administration of 2.7 mg Nalmefene (One OPVEE nasal spray in One Nostril), IN Dose of 5.4 mg Nalmefene (One OPVEE nasal spray in Each Nostril) and IN Dose of 5.4 mg Nalmefene (Two OPVEE nasal sprays in One Nostril)

(a)

(b)

Values represent the mean and standard deviation (n=24)

Absorption

After administration of one 2.7 mg OPVEE nasal spray to healthy adult subjects, the median Tmaxfor OPVEE was 0.250 hours, compared to 0.33 hours for the intramuscular nalmefene.

After administration of two 2.7 mg OPVEE nasal sprays (total dose 5.4mg) to healthy adult subjects, the median Tmaxfor OPVEE was 0.250 hours.

The dose normalized area under the curve (AUC0-inf) to infinity is similar for one 2.7 mg OPVEE nasal spray in one nostril and one 2.7 mg OPVEE nasal spray in each nostril with a geometric mean ratio of 96.23% (90%CI 92.00%-100.65%). The dose normalized AUC0-infis also similar for one 2.7 mg OPVEE nasal spray in one nostril and two 2.7 mg OPVEE nasal sprays in one nostril with a geometric mean ratio of 91.19% (90%CI 87.19%-95.38%).

The mean bioavailability (Frel) of OPVEE was 0.806 relative to intramuscular administration of nalmefene.

Distribution

Following a 1 mg parenteral dose, nalmefene was rapidly distributed. In a study of brain receptor occupancy, a 1 mg dose of nalmefene blocked over 80% of brain opioid receptors within 5 minutes after administration. The apparent volumes of distribution centrally (Vd) and at steady-state (Vss) are 3.9 ± 1.1 L/kg and 8.6 ± 1.7 L/kg, respectively. Ultrafiltration studies of nalmefene have demonstrated that 45% (CV 4.1%) is bound to plasma proteins over a concentration range of 0.1 to 2μg/mL. An in vitro determination of the distribution of nalmefene in human blood demonstrated that nalmefene distributed 67% (CV 8.7%) into red blood cells and 39% (CV 6.4%) into plasma. The whole blood to plasma ratio was 1.3 (CV 6.6%) over the nominal concentration range in whole blood from 0.376 to 30 ng/mL.

Elimination

After administration of 2.7 mg OPVEE nasal spray to healthy adult subjects, plasma concentrations have a terminal elimination half-life of 11.4 (%CV 20.8) hours. The apparent clearance of nalmefene is 75.7 (%CV 23.8) L/hr.

Specific Populations

13 NONCLINICAL TOXICOLOGY

13.1 Carcinogenesis, Mutagenesis, Impairment of Fertility

Carcinogenesis

The carcinogenic potential of nalmefene has not been evaluated.

Mutagenesis

Nalmefene did not have mutagenic activity in the Ames test with five bacterial strains or the mouse lymphoma assay. Clastogenic activity was not observed in the mouse micronucleus test or in the cytogenic bone marrow assay in rats. However, nalmefene did exhibit a weak but significant clastogenic activity in the human lymphocyte metaphase assay in the absence but not in the presence of exogenous metabolic activation.

Impairment of Fertility

Oral administration of nalmefene up to 1200 mg/m^2/day did not affect fertility in rats at exposures at least 6 times the exposure corresponding to a human dose of 5.4 mg (two nalmefene nasal sprays) on an AUC basis.

16 HOW SUPPLIED/STORAGE AND HANDLING

16.1 How Supplied

Each unit-dose nasal spray device delivers 2.7 mg of nalmefene (equivalent to 3 mg of nalmefene hydrochloride) in 0.1 mL. Each carton contains two unit-dose nasal spray devices.

NDC # 12496-0003-2

OPVEE is not made with natural rubber latex.

16.2 Storage and Handling

Store OPVEE nasal spray in the blister and cartons provided.

Store OPVEE nasal spray at controlled room temperature 15°C to 25°C (59°F to 77°F). Short-term excursions permitted between 4°C to 40°C (39°F to 104°F). Do not freeze. Protect from light.

Do not open individual blister packs or test nasal spray devices before use.

Each unit-dose nasal spray device sprays one (1) time and cannot be re-used.

17 PATIENT COUNSELING INFORMATION

Advise the patient and family members or caregivers to read the FDA-approved patient labeling (Patient Information and Instructions for Use).

Recognition of Opioid Overdose

Inform patients and their family members or caregivers about how to recognize the signs and symptoms of an opioid overdose such as the following:

- Extreme somnolence -inability to awaken a patient verbally or upon a firm sternal rub.
- Respiratory depression -this can range from slow or shallow respiration to no respiration in a patient who is unarousable.
- Other signs and symptoms that may accompany somnolence and respiratory depression include the following:
  - Miosis
  - Bradycardia and/or hypotension.

Risk of Recurrent Respiratory Depression

While the duration of action of nalmefene is as long as most opioids, instruct patients and their family members or caregivers that they must seek immediate emergency medical assistance after administration of the first dose of OPVEE and keep the patient under continued surveillance, even after an apparently adequate initial response to OPVEE nasal spray treatment. A second dose may be necessary if there is recurrence of symptoms of opioid overdose [see Dosage and Administration (2.1), Warnings and Precautions (5.1)].

Limited Efficacy for/with Partial Agonists or Mixed Agonist/Antagonists

Instruct patients and their family members or caregivers that the reversal of respiratory depression caused by partial agonists or mixed agonist/antagonists, such as buprenorphine and pentazocine, may be incomplete and may require repeated administration of OPVEE nasal spray, using a new nasal spray device each time [see Dosage and Administration (2.3), Warnings and Precautions (5.2)] .

Precipitation of Severe Opioid Withdrawal

Instruct patients and their family members or caregivers that the use of OPVEE nasal spray in patients who are opioid dependent may precipitate opioid withdrawal [see Warnings and Precautions (5.3), Adverse Reactions (6)] .

Administration Instructions

Instruct patients and their family members or caregivers to:

- Ensure OPVEE is readily available in locations where persons may be intentionally or accidentally exposed to an opioid overdose (i.e., opioid emergencies).
- Use each OPVEE device only one time. Do not test or prime prior to use [see Dosage and Administration (2.1)] .
- Administer OPVEE as quickly as possible if a patient is unresponsive and an opioid overdose is suspected, even when in doubt, because prolonged respiratory depression may result in damage to the central nervous system or death. OPVEE is not a substitute for emergency medical care [see Dosage and Administration (2.1)] .
- Lay the patient on their back and administer OPVEE into one nostril while providing support to the back of the neck to allow the head to tilt back [see Dosage and Administration (2.1)].
- Hold the OPVEE nasal spray device with your fingers on either side of the nozzle and thumb on the white plunger.
- Insert the nozzle into the nose.
- Press the plunger firmly to give a dose in the nose.
- The dose has been delivered when the white plunger has been pushed all the way down until it stops.
- Remove the OPVEE nasal spray from the nose after the dose has been given.
- Call 911 after giving the first dose of OPVEE nasal spray.
- Put the person on their side in the recovery position.
- Watch the person carefully. Wait 2 to 5 minutes to see if the person wakes up.
- If the patient responds by waking up to the voice or touch or starts breathing normally, place them in the recovery position by turning them to their side as shown in the Instructions for Use and call for emergency medical assistance immediately after administration of OPVEE. Additional supportive and/or resuscitative measures may be helpful while awaiting emergency medical assistance [see Dosage and Administration (2.1)] .
- Monitor the patient and re-administer additional doses of OPVEE every 2 to 5 minutes, using a new OPVEE device. If the patient is not responding or responds and then relapses back into respiratory depression, administer OPVEE in alternate nostrils with each dose [see Dosage and Administration (2.1)] .
- Remain with the person until emergency medical help arrives.
- Replace OPVEE before its expiration date.

OPVEE®is a registered trademark of Indivior Inc.
©2023 Indivior Inc. All Rights Reserved.
Manufactured for: Indivior Inc., North Chesterfield, VA, 23235, USA

PATIENT INFORMATION
OPVEE (op vee)
(nalmefene)
nasal spray

You and your family members or caregivers should read this Patient Information leaflet before an opioid emergency happens. This information does not take the place of talking with your healthcare provider about your medical condition or your treatment.

What is the most important information I should know about OPVEE nasal spray?
OPVEE nasal spray is used to temporarily reverse the effects of opioid medicines. The medicine in OPVEE nasal spray is not expected to have an effect in people who are not taking opioid medicines. Always carry OPVEE nasal spray with you in case of an opioid emergency.

1. Use OPVEE nasal spray right away if you or your caregiver think signs or symptoms of an opioid emergency are present, even if you are not sure, because an opioid emergency can cause severe injury or death. Signs and symptoms of an opioid emergency may include:
  - unusual sleepiness and you are not able to awaken the person with a loud voice or rubbing firmly on the middle of their chest (sternum)
  - breathing problems including slow or shallow breathing in someone difficult to awaken or who looks like they are not breathing
  - the black circle in the center of the colored part of the eye (pupil) is very small, sometimes called "pinpoint pupils" in someone difficult to awaken
2. Family members, caregivers, or other people who may have to use OPVEE nasal spray in an opioid emergency should know where OPVEE nasal spray is stored and how to give it before an opioid emergency happens.
3. Call 911 or get emergency medical help right away after giving the first dose of OPVEE nasal spray.Rescue breathing or CPR (cardiopulmonary resuscitation) may be given while waiting for emergency medical help.
4. The signs and symptoms of an opioid emergency can return after OPVEE nasal spray is given. If this happens, give another dose every 2 to 5 minutes using a new OPVEE nasal spray and watch the person closely until emergency help is received.

What is OPVEE nasal spray?

- OPVEE nasal spray is a prescription medicine used in adults and children 12 years of age and older for the treatment of an opioid emergency such as an overdose or a possible opioid overdose with signs of breathing problems and severe sleepiness or not being able to respond.
- OPVEE nasal spray is to be given right away and does not take the place of emergency medical care. Get emergency medical help right way after giving the first dose of OPVEE nasal spray, even if the person wakes up.

It is not known if OPVEE nasal spray is safe and effective in children younger than 12 years of age.

Do not use OPVEE nasal spray if youare allergic to nalmefene or any of the ingredients in OPVEE nasal spray. See the end of this leaflet for a complete list of ingredients in OPVEE nasal spray.

Before using OPVEE nasal spray, tell your healthcare provider about all of your medical conditions, including if you:

- have heart problems
- are pregnant or plan to become pregnant. Use of OPVEE nasal spray may cause withdrawal symptoms in your unborn baby. Your unborn baby should be examined by a healthcare provider right away after you use OPVEE nasal spray.
- are breastfeeding or plan to breastfeed. It is not known if OPVEE nasal spray passes into your breast milk.

Tell your healthcare provider about the medicines you take,including prescription and over-the counter medicines, vitamins, and herbal supplements.

How should I use OPVEE nasal spray?
Read the "Instructions for Use" at the end of this Patient Information leaflet for detailed information about how to use OPVEE nasal spray.

- Use OPVEE nasal spray exactly as prescribed by your healthcare provider.
- Each OPVEE nasal spray only contains 1 dose of medicine and cannot be reused.
- Do not test or prime OPVEE nasal spray before use.
- Lay the person on their back. Use your hand to support behind their neck and allow the head to tilt back before giving OPVEE nasal spray.
- OPVEE nasal spray should be given into one nostril.
- If additional doses are needed, give OPVEE nasal spray in the other nostril.

What are the possible side effects of OPVEE nasal spray?
OPVEE nasal spray may cause serious side effects, including:

- Sudden opioid withdrawal symptoms.In someone who has been using opioids regularly, opioid withdrawal symptoms can happen suddenly after receiving OPVEE nasal spray and may include:

- body aches
- diarrhea
- increased heart rate
- fever
- runny nose
- sneezing

- goose bumps
- sweating
- yawning
- nausea or vomiting
- nervousness
- restlessness or irritability

- shivering or trembling
- stomach cramping
- weakness
- increased blood pressure

- Risk of opioid overdose.OPVEE nasal spray blocks the effects of opioids and may cause opioid withdrawal in someone who has been using opioids regularly. Do nottake large amounts of opioids to try to overcome the opioid-blocking effects of OPVEE nasal spray. This could lead to an opioid overdose and death. Call 911 or get emergency medical help right away after using OPVEE nasal spray.

The most common side effects of OPVEE nasal spray include:

- nose (nasal) discomfort
- headache
- nausea
- dizziness
- hot flush

- vomiting
- anxiety
- tiredness
- nasal congestion
- throat irritation

- pain in the nose
- decreased appetite
- changes in the sense of taste
- skin redness
- increased sweating

These are not all of the possible side effects of OPVEE nasal spray.
Call your doctor for medical advice about side effects. You may report side effects to FDA at 1-800-FDA-1088.

How should I store OPVEE nasal spray?

- Store OPVEE nasal spray at room temperature between 59°F to 77°F (15°C to 25°C).
- Do not freeze OPVEE nasal spray.
- Keep OPVEE nasal spray in its box until ready to use.
- Protect from light.
- Replace OPVEE nasal spray before the expiration date on the box.

Keep OPVEE nasal spray and all medicines out of the reach of children.

General information about the safe and effective use of OPVEE nasal spray.
Medicines are sometimes prescribed for purposes other than those listed in a Patient Information leaflet. Do not use OPVEE nasal spray for a condition for which it was not prescribed. You can ask your pharmacist or healthcare provider for information about OPVEE nasal spray that is written for health professionals.

What are the ingredients in OPVEE nasal spray?
Active ingredient: nalmefene
Inactive ingredients:benzalkonium chloride, disodium ethylenediaminetetraacetate, dodecyl maltoside, sodium chloride, and purified water.
OPVEE nasal spray is not made with natural rubber latex.
OPVEE®is a registered trademark of Indivior Inc.
©2023 Indivior Inc. All Rights Reserved.
Manufactured for: Indivior Inc., North Chesterfield, VA, 23235, USA
For more information, visit www.OPVEE.com or call 1-877-782-6966

This Patient Information has been approved by the U.S. Food and Drug Administration.

Issued: 06/2023

INSTRUCTIONS FOR USE OPVEE (op vee) (nalmefene) nasal spray

The Instructions for Use contains information on how to give OPVEE nasal spray in response to a known or suspected opioid overdose in adults and children 12 years of age and older. You and your family members or caregivers should read the Instructions for Use that comes with OPVEE nasal spray before using it. Talk to your healthcare provider if you and your family members or caregivers have any questions about the use of OPVEE nasal spray.

Important Information You Need to Know Before Giving OPVEE nasal spray

- For use in the nose only.
- Do not remove or test the OPVEE nasal spray before use.
- Each OPVEE nasal spray has 1 dose and cannot be reused.
- You do not need to prime OPVEE nasal spray.

Check for response
Step 1. Shout"wake up" and shakethe person gently.
If there is no response, slow breathing, or no breathing, lay the person flat on their back (Figure A).

Figure A

Prepare to give OPVEE nasal spray
Step 2. Remove OPVEE nasal spray from the box. Peel off the back from the top corner to open the OPVEE nasal spray blister (Figure B).
Step 3. Hold the OPVEE nasal spray with your fingers on both sides of the nozzle and your thumb on the white plunger (Figure C).
Do not press the plunger yet.

Figure B
Figure C

Give OPVEE nasal spray
Step 4.Provide support behind the neck with your hand and tilt the person's head back (Figure D).
Step 5.Gently insert the nozzle into one nostril until your fingers on either side of the nozzle are against the bottom of the person's nose. (Figure D).
Step 6.Press the plunger firmly to give the dose of OPVEE nasal spray in the nose.
The dose has been delivered when the white plunger has been pushed all the way down until it stops.
Step 7.Remove the OPVEE nasal spray from the nostril after the dose has been given.

Figure D

After giving OPVEE nasal spray
Step 8. Call 911or get emergency medical help right away (Figure E).
Step 9. Move the person on their side (recovery position)(Figure F):

- Hand is supporting their head.
- Bend their knee.
- Turn their face to the side.

Step 10. Wait for 2 to 5 minutesto see if the person wakes up. If the person does not respond by waking up, to voice or touch, or start breathing normally, another dose may be given (Figure G).

- Get a new OPVEE nasal sprayfrom the box.
- Repeat Steps 1 through 7 to give another dose of OPVEE in the other nostril.
- If more OPVEE nasal sprays are available, repeat Steps 1 through 7 every 2 to 5 minutes, alternating nostrils, until the person wakes up or medical help arrives.

Stay with the person until medical help arrives.
Step 11.After OPVEE nasal spray has been used, put it back into its box. Throw away (dispose of) the used OPVEE nasal spray in a place that is away from children.

Figure E
Figure F
Figure G

Storing OPVEE nasal spray

- Store OPVEE nasal spray at room temperature between 59°F to 77°F (15°C to 25°C).
- Do not freeze OPVEE nasal spray.
- Keep OPVEE nasal spray in its box until ready to use.
- Protect from light.
- Replace OPVEE nasal spray before the expiration date on the box.

Keep OPVEE nasal spray and all medicines out of the reach of children.

For more information about OPVEE nasal spray, go to www.OPVEE.com or call 1-877-782-6966.

OPVEE®is a registered trademark of Indivior Inc.
©2023 Indivior Inc. All Rights Reserved.
Manufactured for: Indivior Inc., North Chesterfield, VA, 23235, USA

This Instructions for Use has been approved by the U.S. Food and Drug Administration.
Issued: 06/2023

OPVEE®
(nalmefene)
nasal spray

QUICK START GUIDE

Use OPVEE nasal spray for known or suspected opioid overdose in adults and children 12 years of age and older.

- Important:OPVEE nasal spray is for use in the nose only.
- Do not remove or testOPVEE nasal spray before use.
- Each OPVEE nasal spray has 1 dose and cannot be reused.
- You do not need to prime OPVEE nasal spray.

1. Check for response

- Shout"wake up" and shakethe person gently.
- If there is no response, slow breathing, or no breathing, lay the person flat on their back.

2. Prepare

- RemoveOPVEE nasal spray from the box.
- Peeloff the back from the top corner to open the OPVEE nasal spray blister.
- Holdthe OPVEE nasal spray with your fingers on both sides of the nozzle and your thumb on the white plunger.
- Do not press the plunger yet.

3. Give a dose in the nose

- Provide support behind the neck with your hand and tilt the person's head back.
- Gently insert the nozzle into one nostriluntil your fingers on either side of the nozzle are against the bottom of the person's nose.
- Push the plunger firmlyall the way down until it stops to give a dose.

4. Call 911 and place person on their side

- Call 911 or get emergency medical help right away.
- Move the person on their side (recovery position).
- Stay with the person until medical help arrives.

5. Watch and give another dose

- Wait 2 to 5 minutesto see if the person wakes up.
- If the person does not wake up:
  - Get a new OPVEE nasal sprayfrom the box.
  - Give another dosein the other nostril.
  - If more OPVEE nasal sprays are available, repeat Steps 1 through 3 every 2 to 5 minutes, alternating nostrils, until the person wakes up or medical help arrives.

OPVEE®is a registered trademark of Indivior Inc.

©2023 Indivior Inc. All Rights Reserved.

Manufactured for: Indivior Inc., North Chesterfield, VA, 23235, USA

PRINCIPAL DISPLAY PANEL - 2.7 mg Bottle Carton

NDC 12496-0003-2
Rx only

OPVEE®
(nalmefene)
NASAL SPRAY
2.7 mg

FOR USE IN THE NOSE ONLY
DO NOT TEST BEFORE USE

Use for known or suspected opioid overdose
in adults and children 12 years of age and older.

Two Unit-Dose Nasal Spray Devices

Each unit-dose nasal spray device delivers
2.7 mg nalmefene in 0.1 mL solution.

EACH DEVICE SPRAYS ONCE ONLY.

For more information about
OPVEE Nasal Spray, go to
www.OPVEE.com or 1-877-782-6966

Check product expiration date before use.